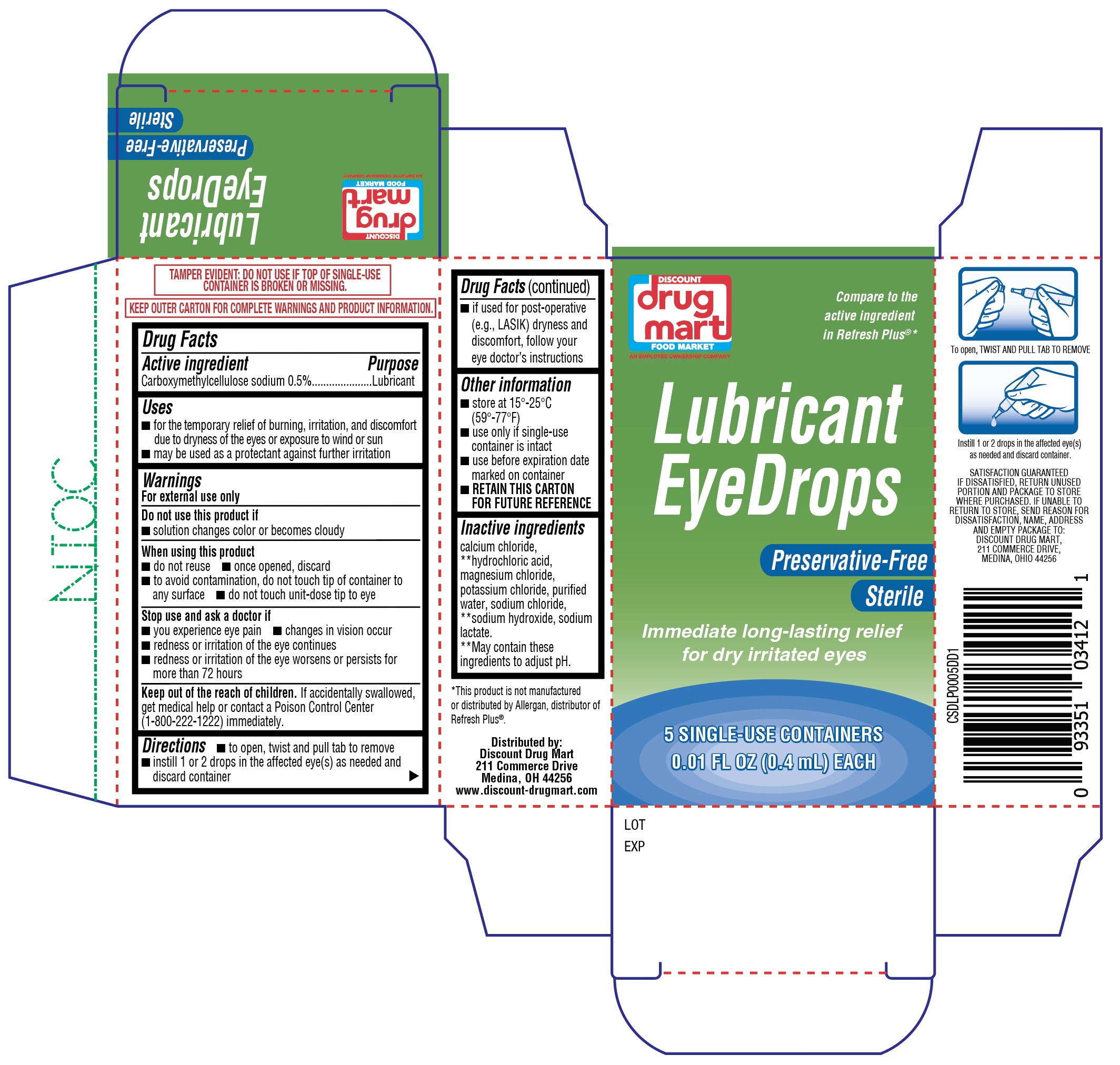 DRUG LABEL: Lubricant Eye Drops
NDC: 55651-510 | Form: SOLUTION/ DROPS
Manufacturer: KC Pharmaceuticals, Inc.
Category: otc | Type: HUMAN OTC DRUG LABEL
Date: 20260225

ACTIVE INGREDIENTS: CARBOXYMETHYLCELLULOSE SODIUM 5 mg/1 mL
INACTIVE INGREDIENTS: WATER; CALCIUM CHLORIDE; MAGNESIUM CHLORIDE; SODIUM CHLORIDE; POTASSIUM CHLORIDE; SODIUM HYDROXIDE; SODIUM LACTATE; HYDROCHLORIC ACID

KC Pharmaceuticals (MFG) labeler NDC for Discount Drug Mart Lubricant Eye Drops 5 ct (PLD) (NDC 53943-510)

ACTIVE INGREDIENT

Carboxymethylcellulose sodium 0.5%

PURPOSE

Eye Lubricant

INDICATIONS AND USAGE

- for the temporary relief of burning, irritation, and discomfort due to dryness of the eye or exposure to wind or sun
- may be used as a protectant against further irritation

Keep out of reach of children. If accidentally swallowed, get medical help or contact a Poison Control Center (1-800-222-1222) immediately.

Directions

- To open, pull and twist tab to remove

- Instill 1 or 2 drops in the affected eye(s) as needed and discard container

INACTIVE INGREDIENT

Calcium Chloride, **Hydrochloric acid, Magnesium Chloride, Potassium Chloride, Purified water, Sodium Chloride, **Sodium Hydroxide, Sodium Lactate. **May contain these ingredients to adjust pH.

Warnings

For external use only

Do not use this product if:

- solution changes color or becomes cloudy

When using this product

- do not reuse
- once opened, discard
- to avoid contamination, do not touch tip of container to any surface
- do not touch unit-dose to eye

Stop use and ask a doctor if you experience any of the following

- you experience eye pain
- changes in vision occur
- redness or irritation of the eye continues
- redness or irritation of the eye gets worse or lasts more than 72 hours